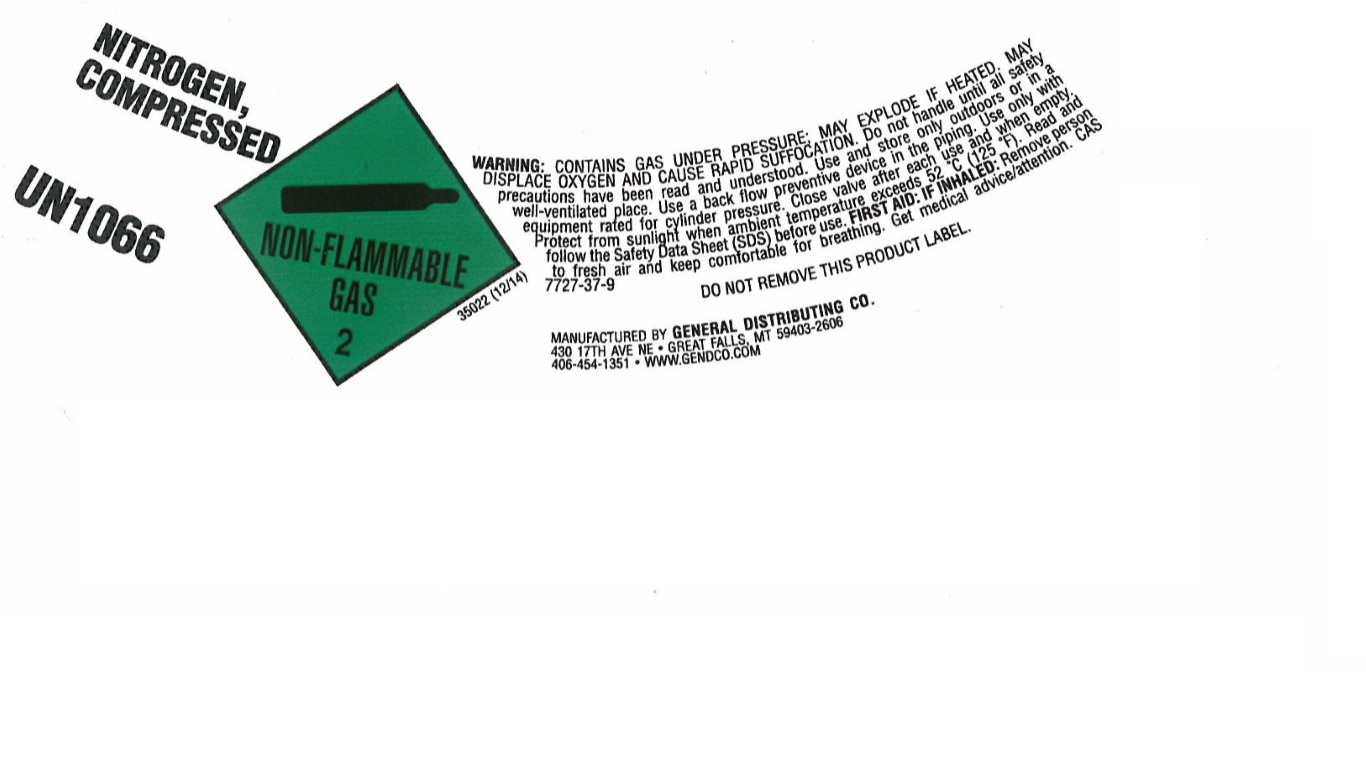 DRUG LABEL: Nitrogen
NDC: 10451-003 | Form: GAS
Manufacturer: General Distributing Company
Category: prescription | Type: HUMAN PRESCRIPTION DRUG LABEL
Date: 20251114

ACTIVE INGREDIENTS: NITROGEN 992 mL/1 L

Nitrogen

PACKAGE LABEL

NITROGEN, COMPRESSED
UN1066
WARNING: CONTAINS GAS UNDER PRESSURE; MAY EXPLODE IF HEATED. MAY DISPLACE OXYGEN AND CAUSE RAPID SUFFOCATION. Do not handle until all safety precautions have been read and understood. Use and store only outdoors or in a well-ventilated place. Use a back flow preventive device in the piping. Use only with equipment rated for cylinder pressure. Close valve after each use and when empty. Protect from sunlight when ambient temperature exceeds 52 C (125 F). Read and follow the Safety Data Sheet (SDS) before use. FIRST AID: IF HEATED: Remove person to fresh air and keep comfortable for breathing. Get medical advice/attention. CAS 7727-37-9
DO NOT REMOVE THIS PRODUCT LABEL.
MANUFACTURED BY GENERAL DISTRIBUTING CO.
430 17TH AVE NE
GREAT FALLS, MY 59403-2606
406-454-1351
WWW.GENDCO.COM